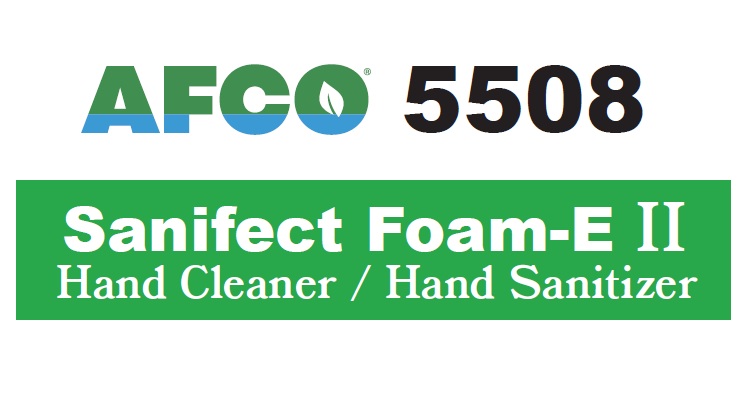 DRUG LABEL: AFCO 5508 Sanifect Foam-E II
NDC: 66949-141 | Form: LIQUID
Manufacturer: Zep Inc.
Category: otc | Type: HUMAN OTC DRUG LABEL
Date: 20251226

ACTIVE INGREDIENTS: CHLOROXYLENOL 2081980 mg/208198 mL
INACTIVE INGREDIENTS: SODIUM LAUROYL SARCOSINATE; COCAMIDOPROPYL HYDROXYSULTAINE; GLYCERIN; WATER; AMMONIUM LAURYL SULFATE; PROPYLENE GLYCOL; EDETATE DISODIUM; ALCOHOL; COCAMIDE MEA; TRIETHYLENE GLYCOL; CITRIC ACID

66949-141 / AF5508 AFCO Sanifect Foam-E II

Active ingredient

Chloroxylenol 1.0% w/w

Purpose

Antibacterial

Uses

- For handwashing to decrease bacteria on the skin.
- Recommended for repeated use.

Warnings

FOR EXTERNAL USE ONLY

When using this product avoid contact with eyes. If contact occurs, rinse eyes thoroughly with water.

Stop use and ask a doctor if if irritation or redness develops and persists.

Keep out of reach of children. If swallowed, get medical help or contact poison control center immediately.

Directions

- Wet hands with water, apply enough product to cover all hand surfaces, rub hands together for at least 30 seconds to work into lather.
- Rinse thoroughly and dry hands completely.

Other information

For Food Processing, Food Service and Professional Use Only.

Inactive ingredients

Water, Ammonium Lauryl Sulfate, Ethanol, Sodium Lauroyl Sarcosinate, Triethylene Glycol, Propylene Glycol, Glycerin, Disodium EDTA, Cocomidopropyl Hydroxysultaine, Citric Acid, Cocamide MIPA.

Questions or comments?

For product or technical information, contact ZEP, INC. Monday to Friday 8 AM to 4 PM EST at 1-877-428-9937 or visit our website at www.zep.com.